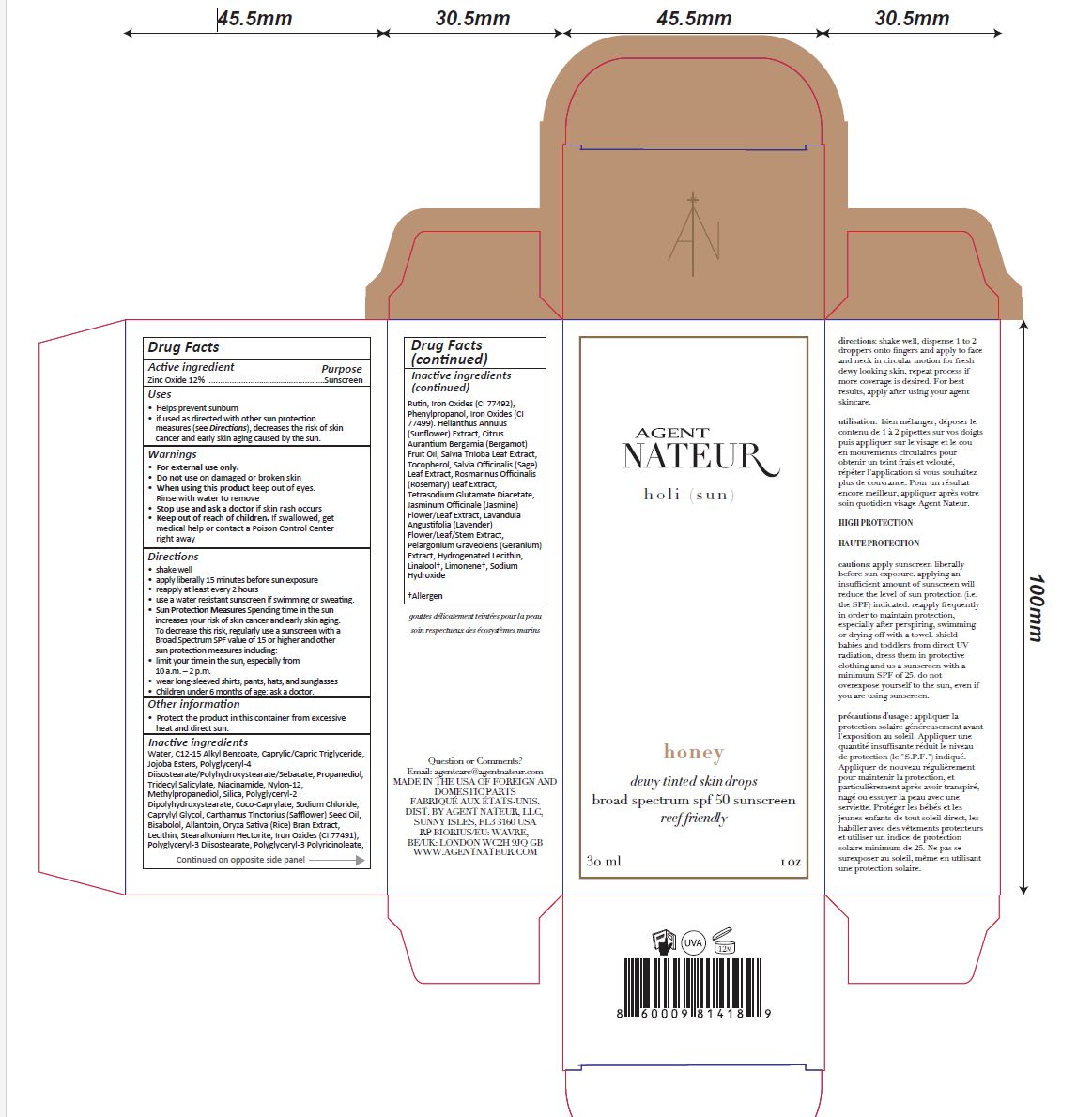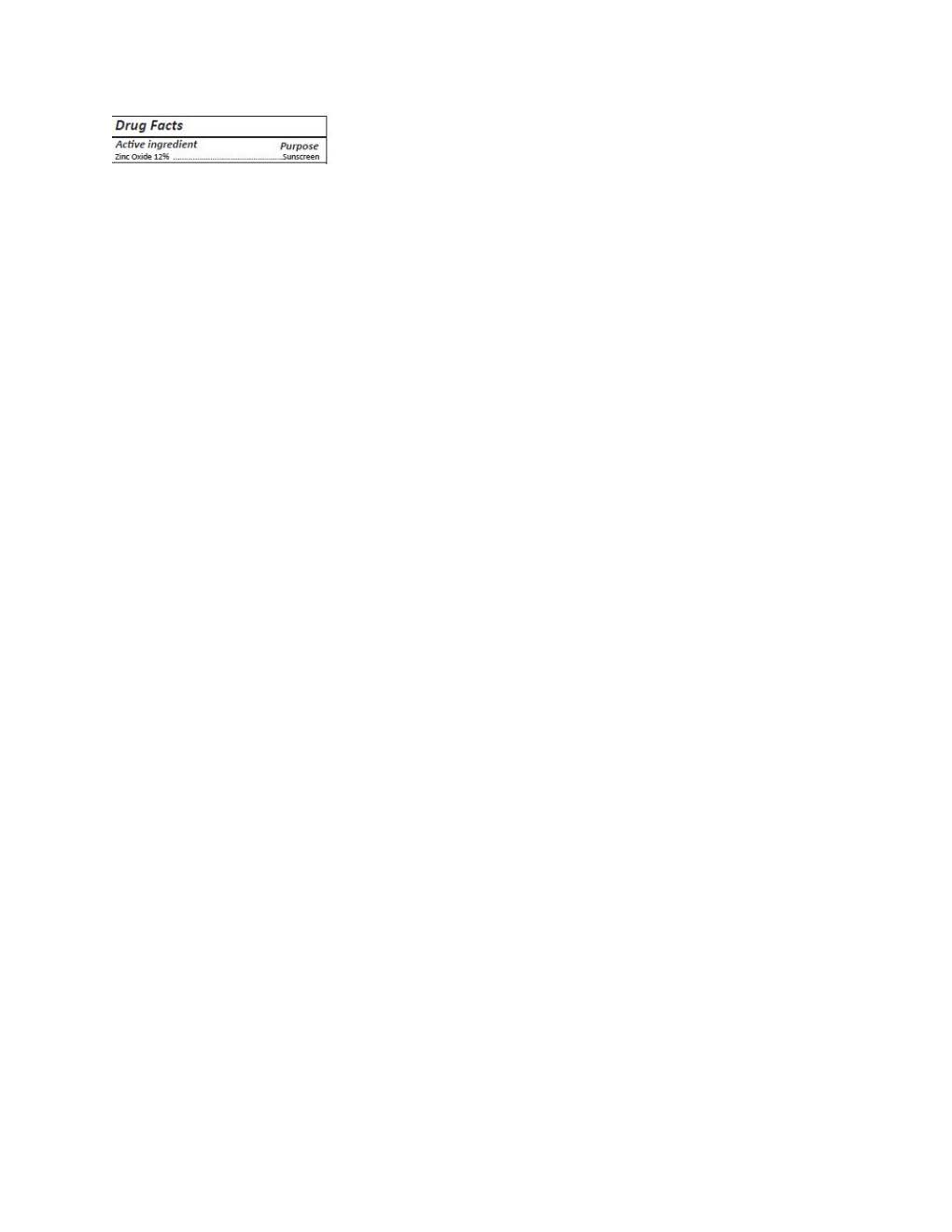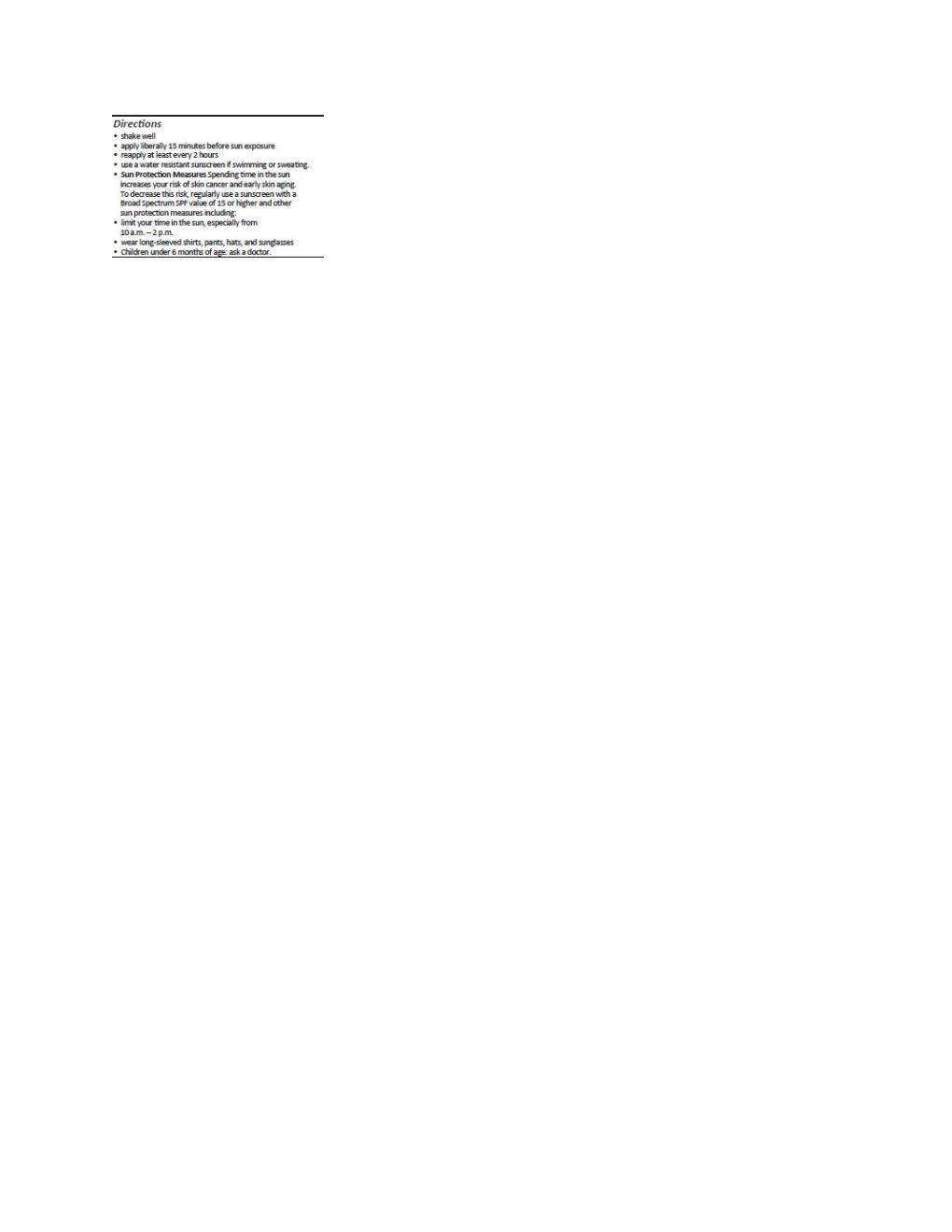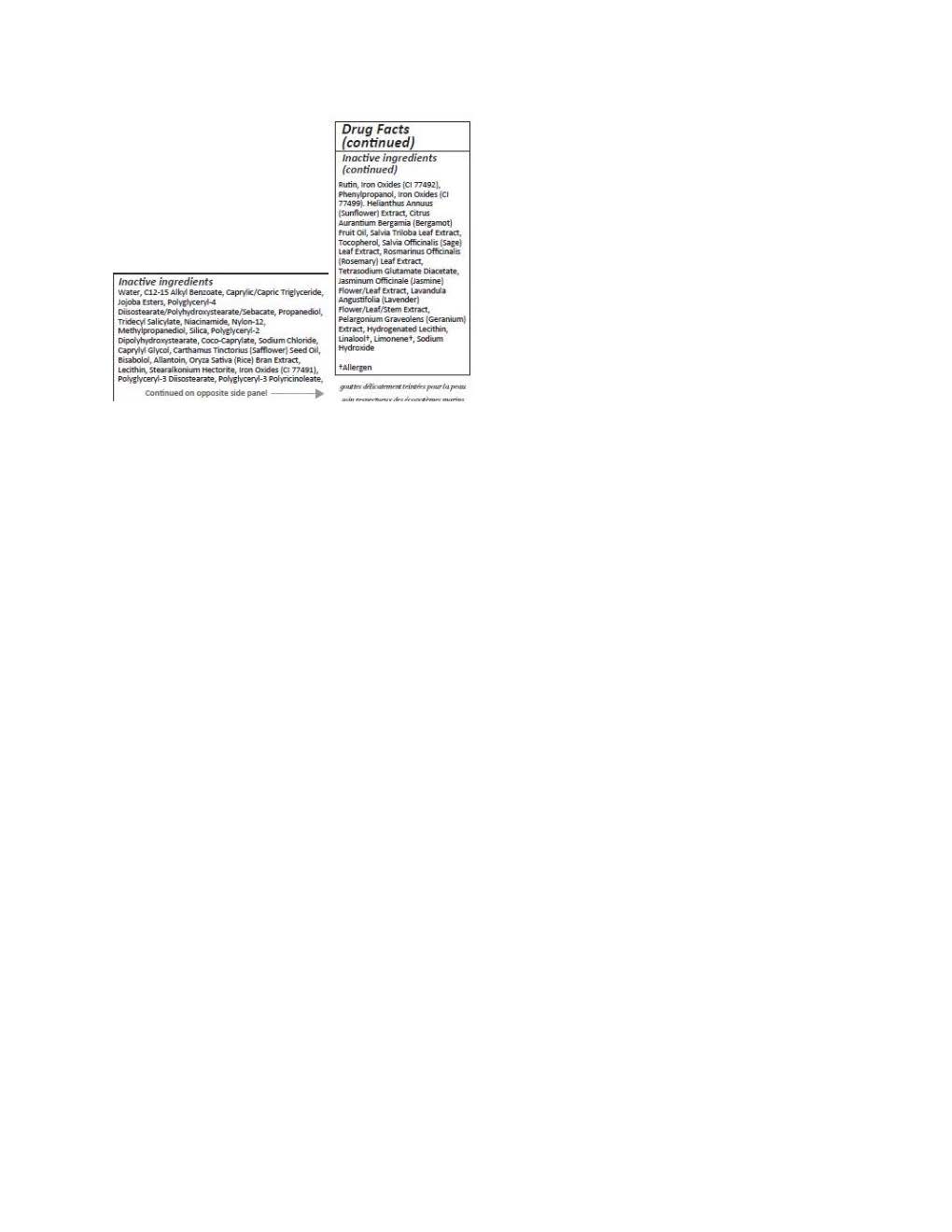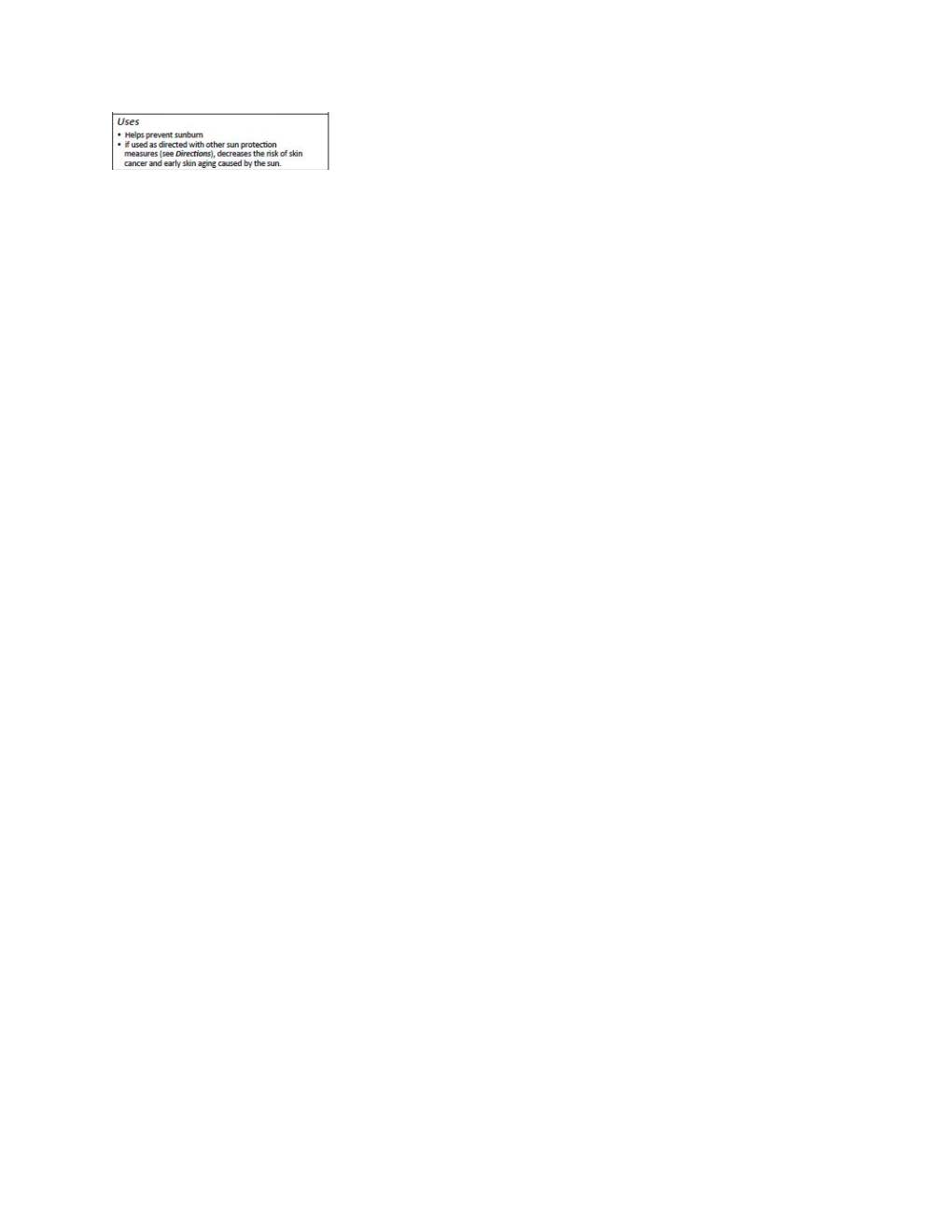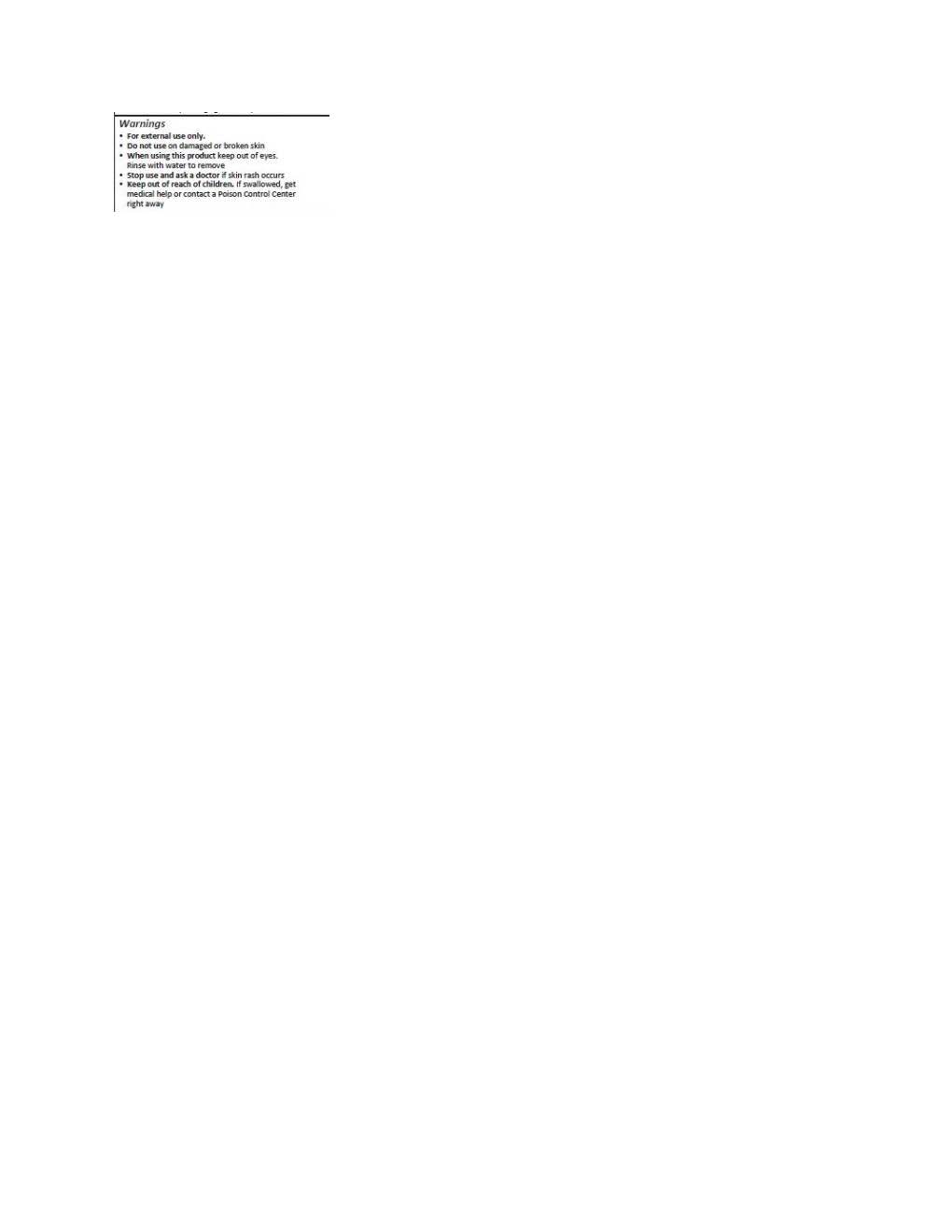 DRUG LABEL: Agent Natuer holi (sun) dewy tinted skin drops
NDC: 83633-2063 | Form: LOTION
Manufacturer: Agent Natuer
Category: otc | Type: HUMAN OTC DRUG LABEL
Date: 20250924

ACTIVE INGREDIENTS: ZINC OXIDE 132 mg/1 mL
INACTIVE INGREDIENTS: RUTIN; JASMINUM OFFICINALE LEAF; HELIANTHUS ANNUUS WHOLE; JOJOBA OIL; ORYZA SATIVA WHOLE; TRIDECYL SALICYLATE; STEARALKONIUM HECTORITE; FERROUS OXIDE; CITRUS AURANTIUM FRUIT OIL; TOCOPHEROL; SALVIA OFFICINALIS FLOWERING TOP; LAVANDULA ANGUSTIFOLIA FLOWERING TOP; PELARGONIUM GRAVEOLENS FLOWER OIL; LINALOOL, (+/-)-; SILICON DIOXIDE; CAPRYLYL GLYCOL; COCO-CAPRYLATE; NYLON-12; PHENYLPROPANOL; LECITHIN, SOYBEAN; METHYLPROPANEDIOL; POLYGLYCERYL-2 DIPOLYHYDROXYSTEARATE; ALLANTOIN; LIMONENE, (+/-)-; ROSMARINUS OFFICINALIS FLOWERING TOP OIL; CARTHAMUS TINCTORIUS SEED OLEOSOMES; POLYGLYCERYL-3 DIISOSTEARATE; ALKYL (C12-15) BENZOATE; .ALPHA.-BISABOLOL, (+)-; SODIUM HYDROXIDE; WATER; NIACINAMIDE; PROPANEDIOL; TETRASODIUM GLUTAMATE DIACETATE; SODIUM CHLORIDE; POLYGLYCERYL-4 DIISOSTEARATE/POLYHYDROXYSTEARATE/SEBACATE

Agent Natuer holi (sun) dewy tinted skin drops